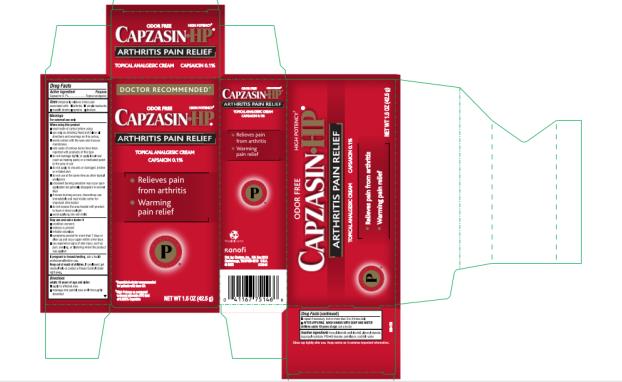 DRUG LABEL: Capzasin HP Arthritis Pain Relief
NDC: 41167-7514 | Form: CREAM
Manufacturer: Chattem, Inc.
Category: otc | Type: HUMAN OTC DRUG LABEL
Date: 20231025

ACTIVE INGREDIENTS: CAPSAICIN 0.001 g/1 g
INACTIVE INGREDIENTS: BENZYL ALCOHOL; CETYL ALCOHOL; GLYCERYL MONOSTEARATE; ISOPROPYL MYRISTATE; PETROLATUM; SORBITOL; WATER; PEG-40 MONOSTEARATE

Capzasin HP Arthritis Pain Relief

Capzasin HP Arthritis Pain Relief

Active Ingredient

Capsaicin 0.1%

Purpose

Topical analgesic

Uses

temporarily relieves minor pain of muscles and joints associated with:

- arthritis
- simple backache
- strains
- sprains
- bruises

Warnings

For external use only

When using this product

- read inside of carton before using
- use only as directed. Read and follow all directions and warnings on this carton/label.
- avoid contact with the eyes and mucous membranes
- rare cases of serious burns have been reported with products of this type
- do not bandage tightly or apply local heat (such as heating pads) or a medicated patch to the area of use
- do not apply to wounds or damaged, broken or irritated skin
- do not use at the same time as other topical analgesics
- a transient burning sensation may occur upon application but generally disappears in several days
- if severe burning occurs, discontinue use immediately and read inside carton for important information
- do not expose the area treated with product to heat or direct sunlight
- avoid applying into skin folds

Stop use and ask a doctor if

- condition worsens
- redness is present
- irritation develops
- symptoms persist for more than 7 days or clear up and occur again within a few days
- you experience signs of skin injury, such as pain, swelling, or blistering where the product was applied

If pregnant or breast-feeding

ask a health professional before use.

Keep out of reach of children.

If swallowed, get medical help or contact a Poison Control Center right away.

Directions

adults and children over 18 years:

- apply to affected area
- massage into painful area until thoroughly absorbed
- repeat as necessary, but no more than 3 to 4 times daily
- WASH HANDS WITH SOAP AND WATER AFTER APPLYING

children 18 years or younger: ask a doctor

Inactive Ingredients

benzyl alcohol, cetyl alcohol, glyceryl stearate, isopropyl myristate, PEG-40 stearate, petrolatum, sorbitol, water (238-10)
READ INFORMATION PRINTED INSIDE CARTON BEFORE USING.

KEEP CARTON AS IT CONTAINS IMPORTANT INFORMATION. Recyclable Carton
Dist. by Chattem, Inc., P.O. Box 2219
Chattanooga, TN 37409-0219 U.S.A.
© 2009 www.chattem.com

Principal Display Panel

Deep Penetrating Odor Free
HIGH POTENCY
CAPZASIN HP®
ARTHRITIS PAIN RELIEF
CAPSAICIN 0.1% TOPICAL ANALGESIC CREME Net wt 1.5 oz (42.5 g)